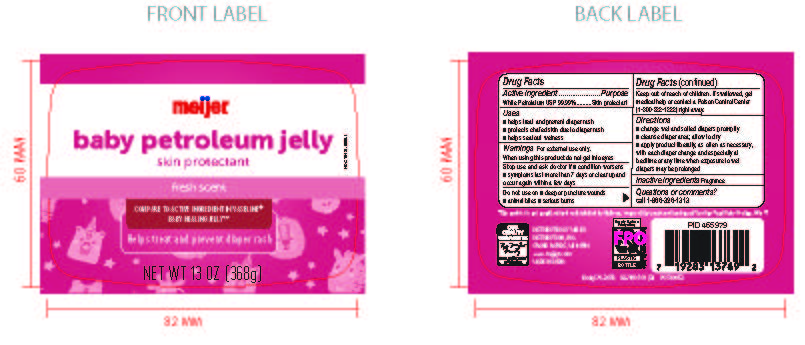 DRUG LABEL: Meijer Baby Petroleum Jelly Skin Protectant Fresh Scent
NDC: 79481-0050 | Form: GEL
Manufacturer: Meijer Distribution
Category: otc | Type: HUMAN OTC DRUG LABEL
Date: 20240826

ACTIVE INGREDIENTS: PETROLATUM 100 g/100 g
INACTIVE INGREDIENTS: FRAGRANCE FRESH CITRUS FLORAL ORC1501495; WATER

Meijer Petroleum Jelly Skin Protectant fresh scent

Active Ingredient

White Petrolatum USP 99.99%

Purpose

Skin Protectant

Uses

■ helps treat and prevent diaper rash
■ protects chafed skin due to diaper rash
■ helps seal out wetness

Warnings

Warnings For external use only.

When using this product do not get into eyes

Stop use and ask doctor if

■ condition worsens
■ symptoms last more than 7 days or clear up and occur again within a few days

Do not use on

■ deep or puncture wounds
■ animal bites ■ serious burns

Keep out of reach of children

If swallowed, get medical help or contact a Poison Control Center (1-800-222-1222) right away.

Directions

■ change wet and soiled diapers promptly
■ cleanse diaper area; allow to dry
■ apply product liberally, as often as necessary, with each diaper change and especially at bedtime or any time when exposure to wet diapers may be prolonged

Inactive Ingredients

Fragrance

Questions

Questions or comments?
call 1-866-326-1313